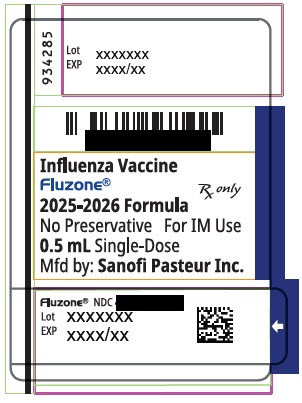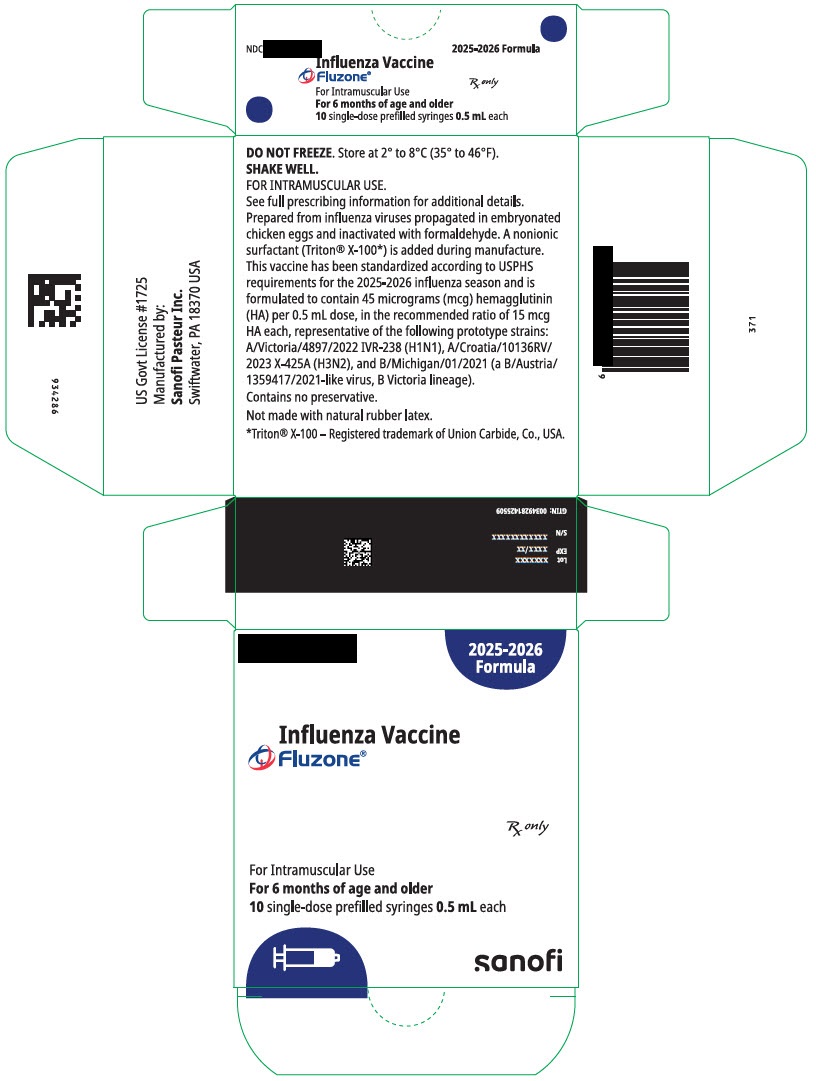 DRUG LABEL: FLUZONE TRIVALENT NORTHERN HEMISPHERE
NDC: 83703-083 | Form: INJECTION, SUSPENSION
Manufacturer: Bamboo US BidCo LLC
Category: other | Type: VACCINE LABEL
Date: 20260202

ACTIVE INGREDIENTS: INFLUENZA A VIRUS A/VICTORIA/4897/2022 IVR-238 (H1N1) ANTIGEN (FORMALDEHYDE INACTIVATED) 15 ug/0.5 mL; INFLUENZA A VIRUS A/CROATIA/10136RV/2023 X-425A (H3N2) ANTIGEN (FORMALDEHYDE INACTIVATED) 15 ug/0.5 mL; INFLUENZA B VIRUS B/MICHIGAN/01/2021 ANTIGEN (FORMALDEHYDE INACTIVATED) 15 ug/0.5 mL
INACTIVE INGREDIENTS: OCTOXYNOL-9; SODIUM PHOSPHATE, DIBASIC, ANHYDROUS; SODIUM PHOSPHATE, MONOBASIC, ANHYDROUS; WATER; FORMALDEHYDE

Fluzone (Influenza Vaccine)
injectable suspension, for intramuscular use
2025–2026 Formula
Initial U.S. Approval: 1980

PRINCIPAL DISPLAY PANEL - 0.5 mL Syringe Label

Influenza Vaccine

Fluzone®
Rx only

2025-2026 Formula

No Preservative
For IM Use

0.5 mL Single-Dose

Mfd by: Sanofi Pasteur Inc.

PRINCIPAL DISPLAY PANEL - 0.5 mL Syringe Package

2025-2026

Formula

Influenza Vaccine
Fluzone®

Rx only

For Intramuscular Use
For 6 months of age and older
10 single-dose prefilled syringes 0.5 mL each

sanofi